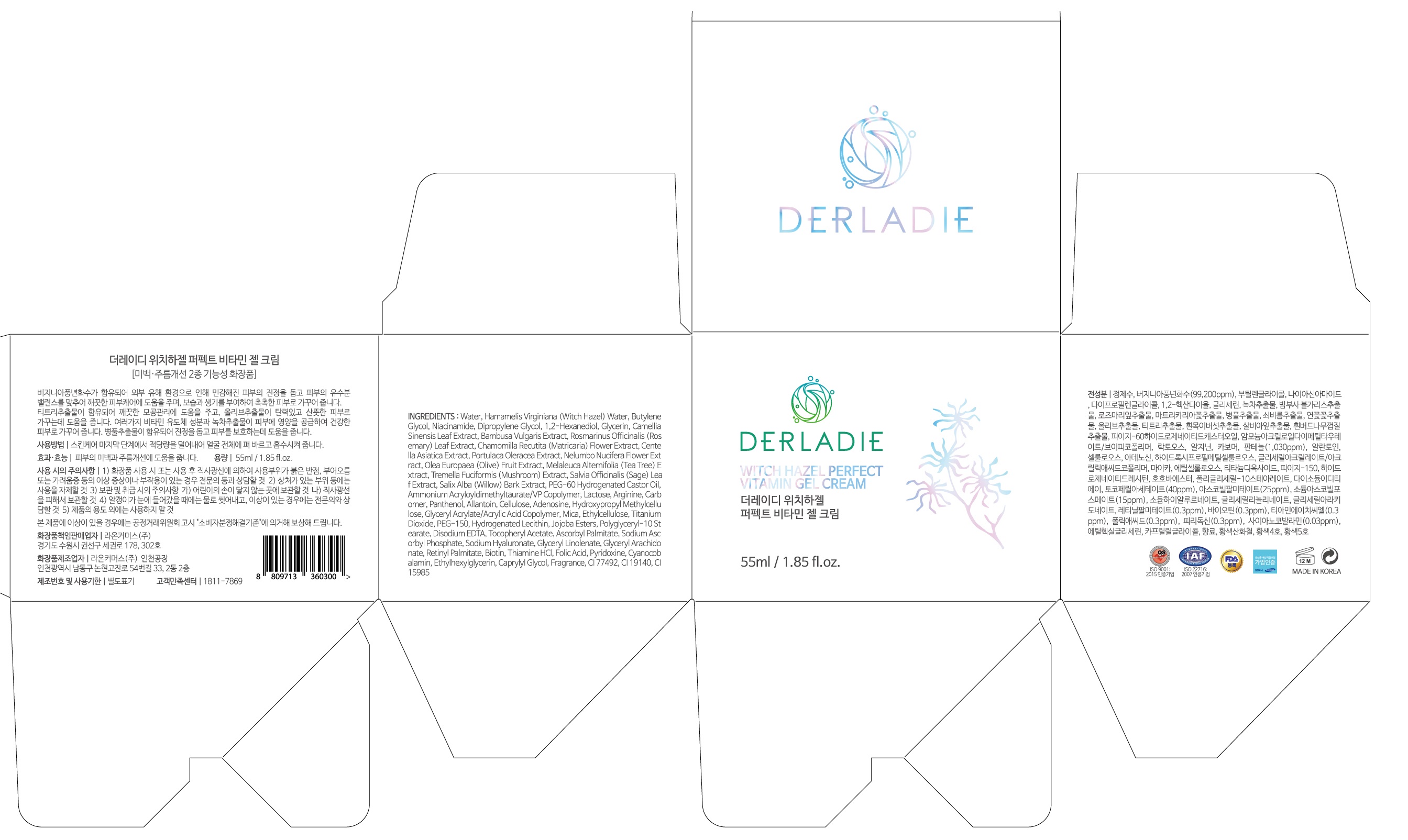 DRUG LABEL: DERLADIE WITCH HAZEL PERFECT VITAMIN GELCREAM
NDC: 82083-0001 | Form: CREAM
Manufacturer: LAON COMMERCE co ltd
Category: otc | Type: HUMAN OTC DRUG LABEL
Date: 20210718

ACTIVE INGREDIENTS: ADENOSINE 0.04 g/100 mL; NIACINAMIDE 2 g/100 mL
INACTIVE INGREDIENTS: WATER

ACTIVE INGREDIENT

niacinamide, allantoin

INACTIVE INGREDIENT

Water
Hamamelis Virginiana (Witch Hazel) Water
Butylene Glycol
Niacinamide
Dipropylene Glycol
1,2-Hexanediol
Glycerin
Camellia Sinensis Leaf Extract
Bambusa Vulgaris Extract
Rosmarinus Officinalis (Rosemary) Leaf Extract
Chamomilla Recutita (Matricaria) Flower Extract
Centella Asiatica Extract
Portulaca Oleracea Extract
Nelumbo Nucifera Flower Extract
Olea Europaea (Olive) Fruit Extract
Melaleuca Alternifolia (Tea Tree) Extract
Tremella Fuciformis (Mushroom) Extract
Salvia Officinalis (Sage) Leaf Extract
Salix Alba (Willow) Bark Extract
PEG-60 Hydrogenated Castor Oil
Ammonium Acryloyldimethyltaurate/VP Copolymer
Lactose
Arginine
Carbomer
Panthenol
Allantoin
Cellulose
Adenosine
Hydroxypropyl Methylcellulose
Glyceryl Acrylate/Acrylic Acid Copolymer
Mica
Ethylcellulose
Titanium Dioxide
PEG-150
Hydrogenated Lecithin
Jojoba Esters
Polyglyceryl-10 Stearate
Disodium EDTA
Tocopheryl Acetate
Ascorbyl Palmitate
Sodium Ascorbyl Phosphate
Sodium Hyaluronate
Glyceryl Linolenate
Glyceryl Arachidonate
Retinyl Palmitate
Biotin
Thiamine HCl
Folic Acid
Pyridoxine
Cyanocobalamin
Ethylhexylglycerin
Caprylyl Glycol
Fragrance
CI 77492
CI 19140
CI 15985

PURPOSE

Skin whitening, wrinkle care

WARNINGS

■ if following abnormal symptoms persist, discontinue use

Irritation around the eyes, ears, mucous membranes, including the mouth, under the skin irritation and rashes

■ Stop immediately and consult a doctor if you experience

1) Hypersensitivity symptoms such as erythema, itching and dermatitis.

2) Skin Irritation

3) Following Instructions when using medication

(1) For external use only (Do not use internally)

(2) Avoid getting into the eyes (if contact occurs, wash well with clean water)

Keep Out of Reach of Children.

INDICATIONS AND USAGE

apply where needed

DOSAGE AND ADMINISTRATION

for external use only